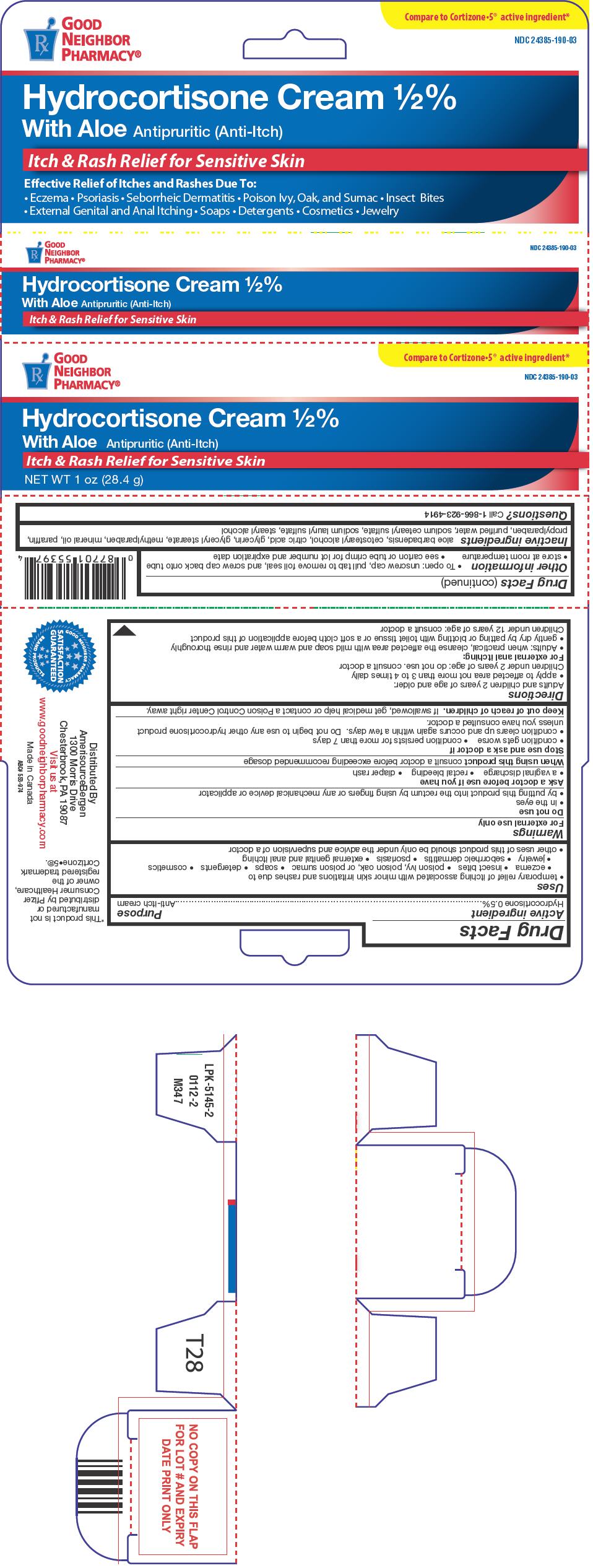 DRUG LABEL: Good Neighbor Pharmacy

NDC: 24385-190 | Form: CREAM
Manufacturer: AmerisourceBergen
Category: otc | Type: HUMAN OTC DRUG LABEL
Date: 20250710

ACTIVE INGREDIENTS: HYDROCORTISONE 0.5 g/100 g
INACTIVE INGREDIENTS: CETOSTEARYL ALCOHOL; CITRIC ACID MONOHYDRATE; GLYCERIN; GLYCERYL MONOSTEARATE; METHYLPARABEN; MINERAL OIL; PARAFFIN; PROPYLPARABEN; WATER; SODIUM CETOSTEARYL SULFATE; SODIUM LAURYL SULFATE; STEARYL ALCOHOL

Good Neighbor Pharmacy®
Hydrocortisone ½% With Aloe for Sensitive Skin

Drug Facts

Active ingredient

Hydrocortisone 0.5%

Purpose

Anti-itch cream

Uses

- temporary relief of itching associated with minor skin irritations and rashes due to
  - eczema
  - insect bites
  - poison ivy, poison oak, or poison sumac
  - soaps
  - detergents
  - cosmetics
  - jewelry
  - seborrheic dermatitis
  - psoriasis
  - external genital and anal itching
- other uses of this product should be only under the advice and supervision of a doctor

Warnings

For external use only

Do not use

- in the eyes
- by putting this product into the rectum by using fingers or any mechanical device or applicator

Ask a doctor before use if you have

- a vaginal discharge
- rectal bleeding
- diaper rash

WHEN USING

When using this productconsult a doctor before exceeding recommended dosage

Stop use and ask a doctor if

- condition gets worse
- condition persists for more than 7 days
- condition clears up and occurs again within a few days. Do not begin to use any other hydrocortisone product unless you have consulted a doctor.

Keep out of reach of children.If swallowed, get medical help or contact a Poison Control Center right away.

Directions

Adults and children 2 years of age and older:

- apply to affected area not more than 3 to 4 times daily

Children under 2 years of age: do not use. consult a doctor

For external anal itching

- Adults: when practical, cleanse the affected area with mild soap and warm water and rinse thoroughly
- gently dry by patting or blotting with toilet tissue or a soft cloth before application of this product

Children under 12 years of age: consult a doctor

Other information

- To open: unscrew cap, pull tab to remove foil seal, and screw cap back onto tube
- store at room temperature
- see carton or tube crimp for lot number and expiration date

Inactive ingredients

aloe barbadensis, cetostearyl alcohol, citric acid, glycerin, glyceryl stearate, methylparaben, mineral oil, paraffin, propylparaben, purified water, sodium cetearyl sulfate, sodium lauryl sulfate, stearyl alcohol

Questions?

Call 1-866-923-4914

Distributed By
AmerisourceBergen
1300 Morris Drive
Chesterbrook, PA 19087

PRINCIPAL DISPLAY PANEL - 28.4 g Tube Carton

Compare to Cortizone•5®active ingredient*

Rx
GOOD
NEIGHBOR
PHARMACY®

NDC 24385-190-03

Hydrocortisone Cream ½%
With Aloe Antipruritic (Anti-Itch)

Itch & Rash Relief for Sensitive Skin

NET WT 1 oz (28.4 g)